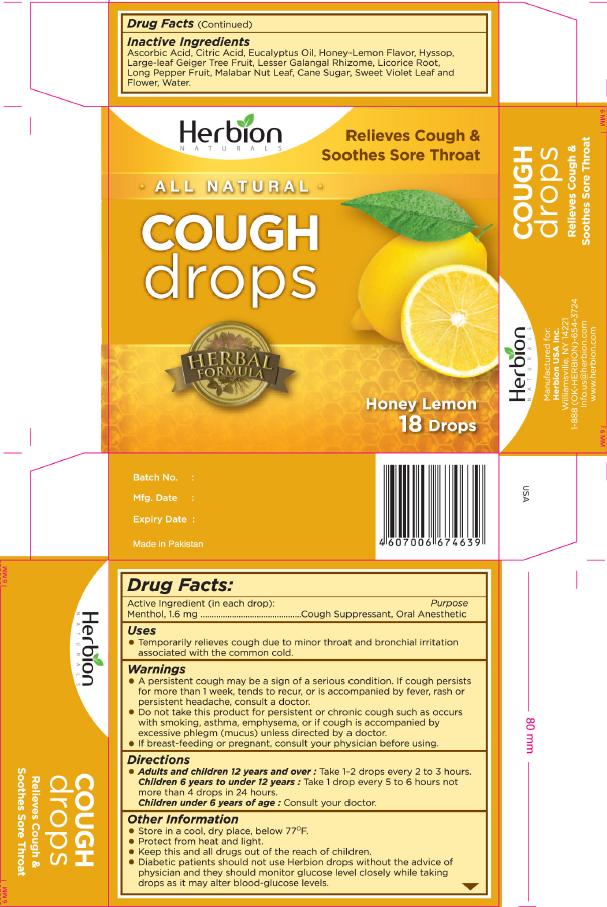 DRUG LABEL: Herbion Naturals
NDC: 44237-008 | Form: LOZENGE
Manufacturer: Herbion Pakistan (Pvt.) Ltd.
Category: otc | Type: HUMAN OTC DRUG LABEL
Date: 20121205

ACTIVE INGREDIENTS: MENTHOL 1.6 mg/1 1
INACTIVE INGREDIENTS: ASCORBIC ACID; CITRIC ACID MONOHYDRATE; EUCALYPTUS OIL; HYSSOPUS OFFICINALIS FLOWERING TOP; LESSER GALANGAL ROOT; LICORICE; LONG PEPPER; JUSTICIA ADHATODA LEAF; SUCROSE; VIOLA ODORATA LEAF; WATER

Active Ingredient (in each drop)

Menthol, 1.6 mg

Purpose

Cough Suppresant, Oral Anesthetic

Uses

- Temporarily relieves cough due to minor throat and bronchial irritation associated with the common cold.

Warnings

- A persistent cough may be a sign of a serious condition. If cough persists for more than 1 week, tends to recur, or is accompanied by fever, rash, or persistent headache, consult a doctor.
- Do not take this product for persistent or chronic cough such as occurs with smoking, asthma, emphysema, or if cough is accompanied by excessive phlegm (mucus) unless directed by a doctor.
- If breast-feeding or pregnant, consult your physician before using.

KEEP OUT OF REACH OF CHILDREN

- Keep this and all drugs out of the reach of children.

Directions

Adults and children 12 years and over: Take 1-2 drops every 2 to 3 hours.
Children 6 years to under 12 years: Take 1 drop every 5 to 6 hours not more than 4 drops in 24 hours
Children under 6 years of age: Consult your doctor.

Other Information

- Store in a cool, dry place, below 77 degrees F.
- Protect from heat and light.
- Diabetic patients should not use Herbion drops without the advice of physician and they should monitor glucose level closely while taking drops as it may alter blood-glucose levels.

Inactive Ingredients

Ascorbic Acid, Citric Acid, Eucalyptus Oil, Honey-Lemon Flavor, Hyssop, Large-leaf Geiger Tree Fruit, Lesser Galangal Rhizome, Licorice Root, Long Pepper Fruit, Malabar Nut Leaf, Cane Sugar, Sweet Violet Leaf and Flower, Water

Side Panel:

Manufactured for:
Herbion USA Inc.
Williamsville, NY 14221
1-888-(OK-HERBION)-654-3724
Info.us@herbion.com
www.herbion.com

Principal Display Panel:

Herbion Naturals

Relieves Cough and Soothes Sore Throat

All Natural

Cough Drops

Herbal Formula

Honey Lemon

18 Drops